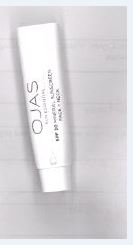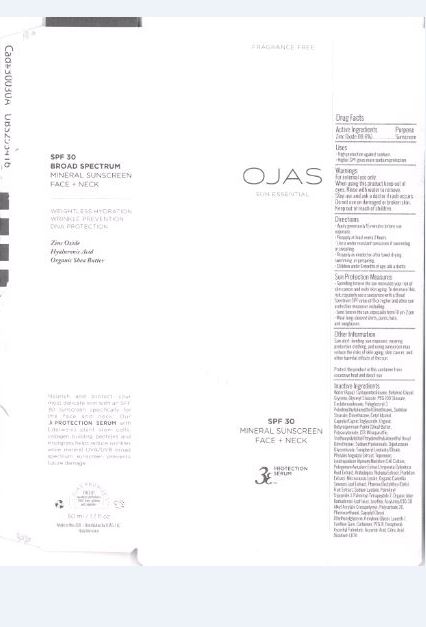 DRUG LABEL: SPF 30 Mineral Sunscreen Face Neck
NDC: 62742-4086 | Form: CREAM
Manufacturer: Allure Labs Inc
Category: otc | Type: HUMAN OTC DRUG LABEL
Date: 20160711

ACTIVE INGREDIENTS: ZINC OXIDE 186 mg/1 mL
INACTIVE INGREDIENTS: WATER; CYCLOMETHICONE 5; BUTYLENE GLYCOL; GLYCERIN; GLYCERYL MONOSTEARATE; PEG-100 STEARATE; CYCLOMETHICONE 6; POLYGLYCERYL-3 POLYDIMETHYLSILOXYETHYL DIMETHICONE (4000 MPA.S); SORBITAN MONOSTEARATE; DIMETHICONE; CETYL ALCOHOL; MEDIUM-CHAIN TRIGLYCERIDES; SHEA BUTTER; POLYACRYLAMIDE (10000 MW); C13-14 ISOPARAFFIN; HYALURONATE SODIUM; GLYCYRRHIZINATE DIPOTASSIUM; PHYSALIS ANGULATA; TEPRENONE; LEONTOPODIUM ALPINUM FLOWERING TOP; POLYGONUM AVICULARE TOP; IMPERATA CYLINDRICA ROOT; ARABIDOPSIS THALIANA; CAMELLIA SINENSIS FLOWER; PHOENIX RECLINATA FRUIT; SODIUM LACTATE; PALMITOYL TRIPEPTIDE-1; PALMITOYL TETRAPEPTIDE-7; ALOE VERA LEAF; LECITHIN, SOYBEAN; CARBOMER COPOLYMER TYPE A (ALLYL PENTAERYTHRITOL CROSSLINKED); POLYSORBATE 20; PHENOXYETHANOL; CAPRYLYL GLYCOL; ETHYLHEXYLGLYCERIN; HEXYLENE GLYCOL; LAURETH-7; XANTHAN GUM; CARBOXYPOLYMETHYLENE; POLYETHYLENE GLYCOL 400; TOCOPHEROL; ASCORBYL PALMITATE; ASCORBIC ACID; CITRIC ACID MONOHYDRATE; EDETATE DISODIUM

DRUG FACTS

Active Ingredients: Zinc Oxide - 18.6%

Purpose: Sunscreen

Uses:

- High protection against sunburn.
- Higher SPF gives more sunburn protection.
- Sun Protection Measures: Spending time in the sun increases your risk of skin cancer and early skin aging. To decrease this risk, regularly use a sunscreen with a broad spectrum SPF value of 15 or higher and other sun protection measures including:
- Limit time in the sun, especially from 10am - 2pm.
- Wear long sleeved shirts, pants, hats and sunglasses.

Warnings: For external use only.

When using this product keep out of eyes.Rinse with water to remove.

Stop use and ask a doctor if rash occurs. Do not use on damaged or broken skin.

Keep out of reach of children

Directions:

- Apply generously 15 minutes before su exposure.
- Reapply at least every 2 hours.
- Use a water resistant sunscreen if swimming or sweating.
- Reapply as needed or after towel drying, swimming or perspiring.
- Children under 6 months of age: ask a doctor.

Other Information

- Sun Alert: limiting sun exposure, wearing protective clothing and using sunscreen may reduce the risk of skin aging, skin cancer and other harmful effects of the sun.

STORAGE AND HANDLING

Protect the product in this container from excessive heat and direct sun.

INACTIVE INGREDIENT

Water (Aqua), Cyclopentasiloxane, Butylene Glycol, Glycerin, Glyceryl Stearate, PEG-100 Stearate, Cyclohexasiloxane, Polyglyceryl-3 Polydimethylsiloxyethyl Dimethicone, Sorbitan Stearate, Dimethicone, Cetyl Alcohol, Caprylic/Capric Triglyceride, Organic Butyrospermum Parkii (Shea) Butter, Polyacrylamide, C13-14 Isoparaffin, Triethoxysilylethyl Polydimethylsiloxyethyl Hexyl Dimethicone, Sodium Hyaluronate, Dipotassium Glycyrrhizate, Tocopheryl Linoleate/Oleate, Physalis Angulata Extract, Teprenone, Leontopodium Alpinum Meristem Cell Culture, Polygonum Aviculare Extract, Imperata Cylindrica Root Extract, Arabidopsis Thaliana Extract, Plankton Extract, Micrococcus Lysate, Organic Camellia Sinensis Leaf Extract, Phoenix Dactylifera (Date) Fruit Extract, Sidium Lactete, Palmitoyl Tripeptide-1, Palmitoyl Tetrapeptide-7, Organic Aloe Barbadensis Leaf Juice, Lecithin, Acrylates/C10-30 Alkyl Acrylate Crosspolymer, Polysorbate-20, Phenoxyethanol, Caprylyl Glycol, Ethylhexylglycerin, Hexylene Glycol, Laureth-7, Xanthan Gum, Carbomer, PEG-8, Tocopherol, Ascorbyl Palmitate, Ascorbic Acid, Citric Acid, Disodium EDTA.

PACKAGE LABEL

Made in USA

Distributed by OJAS, LLC

OjasSkin.com